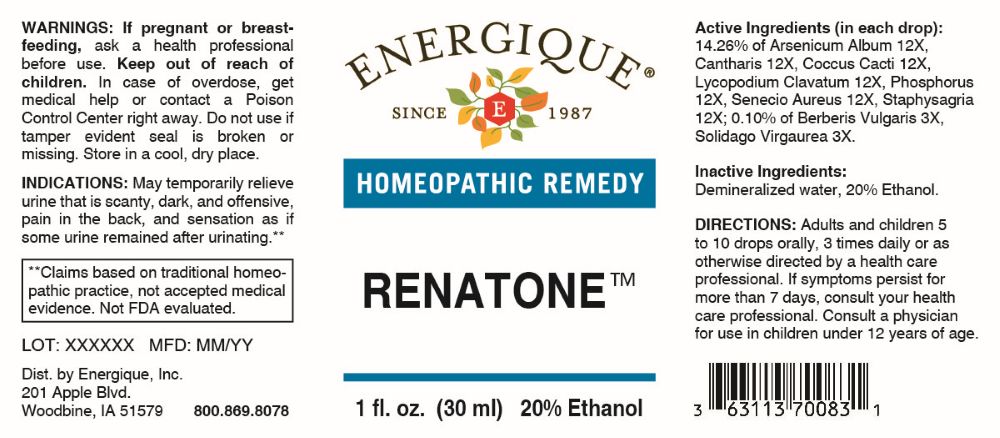 DRUG LABEL: Renatone
NDC: 44911-0904 | Form: LIQUID
Manufacturer: Energique, Inc.
Category: homeopathic | Type: HUMAN OTC DRUG LABEL
Date: 20260227

ACTIVE INGREDIENTS: BERBERIS VULGARIS ROOT BARK 3 [hp_X]/1 mL; SOLIDAGO VIRGAUREA FLOWERING TOP 3 [hp_X]/1 mL; LYTTA VESICATORIA 12 [hp_X]/1 mL; ARSENIC TRIOXIDE 12 [hp_X]/1 mL; PROTORTONIA CACTI 12 [hp_X]/1 mL; LYCOPODIUM CLAVATUM SPORE 12 [hp_X]/1 mL; PHOSPHORUS 12 [hp_X]/1 mL; PACKERA AUREA WHOLE 12 [hp_X]/1 mL; STAPHISAGRIA MACROSPERMA SEED 12 [hp_X]/1 mL
INACTIVE INGREDIENTS: WATER; ALCOHOL

DRUG FACTS:

ACTIVE INGREDIENTS:

(in each drop): 14.26% of Arsenicum Album 12X, Cantharis 12X, Coccus Cacti 12X, Lycopodium Clavatum 12X, Phosphorus 12X, Senecio Aureus 12X, Staphysagria 12X; 0.10% of Berberis Vulgaris 3X, Solidago Virgaurea 3X.

PURPOSE:

May temporarily relieve urine that is scanty, dark, and offensive, pain in the back, and sensation as if some urine remained after urinating.**

**Claims based on traditional homeopathic practice, not accepted medical evidence. Not FDA evaluated.

WARNINGS:

If pregnant or breast-feeding, ask a health professional before use.

Keep out of reach of children. In case of overdose, get medical help or contact a Poison Control Center right away.

Do not use if tamper evident seal is broken or missing. Store in a cool, dry place.

KEEP OUT OF REACH OF CHILDREN:

In case of overdose, get medical help or contact a Poison Control Center right away.

DIRECTIONS:

Adults and children 5 to 10 drops orally, 3 times daily or as otherwise directed by a health care professional. If symptoms persist for more than 7 days, consult your health care professional. Consult a physician for use in children under 12 years of age.

USES:

May temporarily relieve urine that is scanty, dark, and offensive, pain in the back, and sensation as if some urine remained after urinating.**

**Claims based on traditional homeopathic practice, not accepted medical evidence. Not FDA evaluated.

INACTIVE INGREDIENTS:

Demineralized water, 20% Ethanol.

QUESTIONS:

Dist. by Energique, Inc.

201 Apple Blvd.

Woodbine, IA 51579

800-869-8078

PACKAGE LABEL DISPLAY:

ENERGIQUE

SINCE 1987

HOMEOPATHIC REMEDY

RENATONE

1 fl. oz. (30 ml)